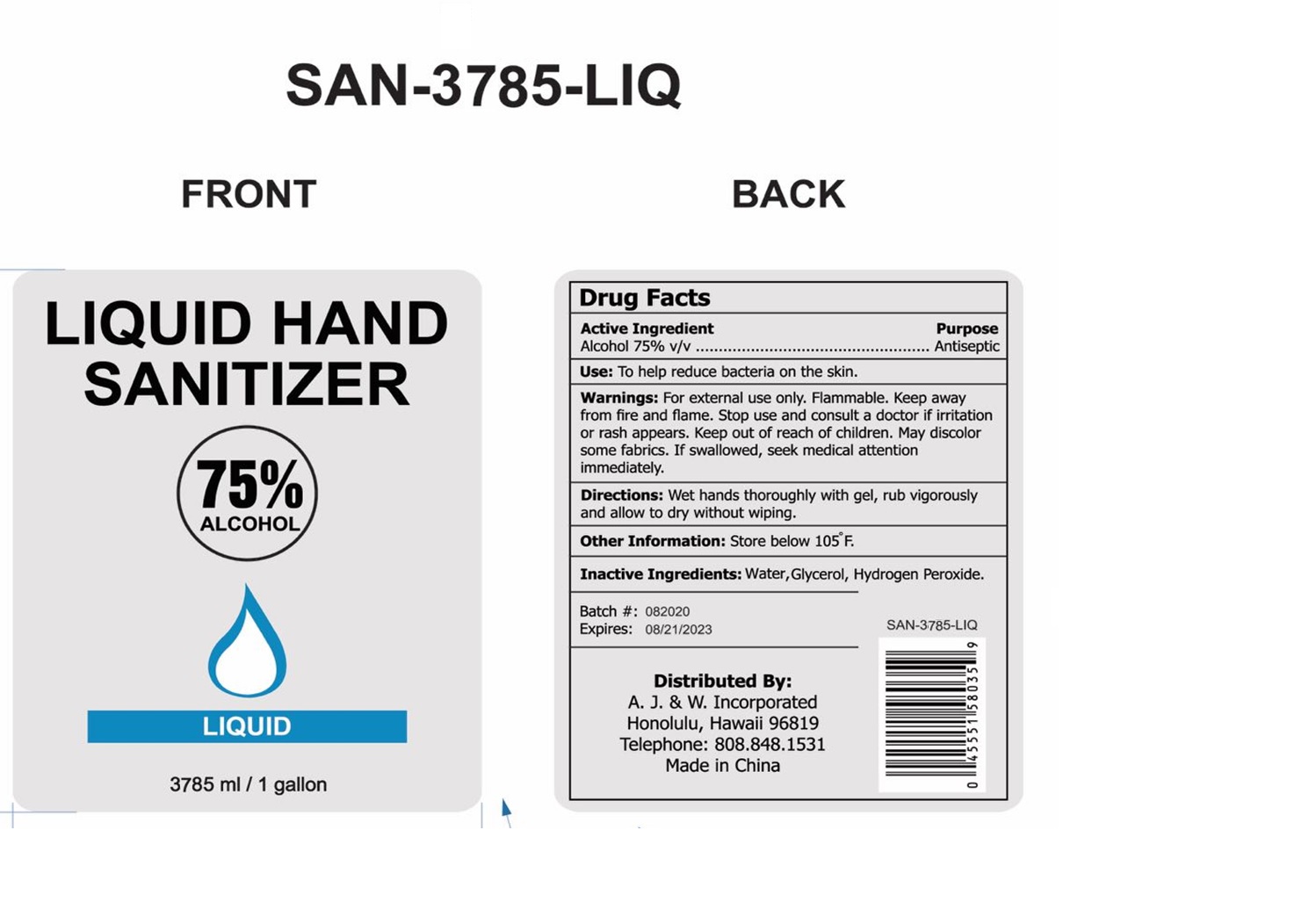 DRUG LABEL: Liquid Hand Sanitizer
NDC: 75742-015 | Form: LIQUID
Manufacturer: Zhejiang Guoyao Jingyue Aerosol Co., Ltd.
Category: otc | Type: HUMAN OTC DRUG LABEL
Date: 20200915

ACTIVE INGREDIENTS: ALCOHOL 75 mL/100 mL
INACTIVE INGREDIENTS: WATER; HYDROGEN PEROXIDE; GLYCERIN

Liquid Hand Sanitizer

Active Ingredient

Alcohol 75% v/v

Purpose

Antiseptic

Uses

To help reduce bacteria on the skin.

Warnings

For external use only. Flammable, keep away from fire and flame. May discolor certain fabrics

Stop use and consult a doctor if irritation or rash appears.

Keep out of reach of children.

DO NOT USE

If swallowed, seek medical attention immediately.

Directions

Wet hands thoroughly with gel, rub vigorously and allow to dry without wiping

Other information

Store below 105°F.

INACTIVE INGREDIENTS:

Water, Glycerin, Hydrogen Peroxide.